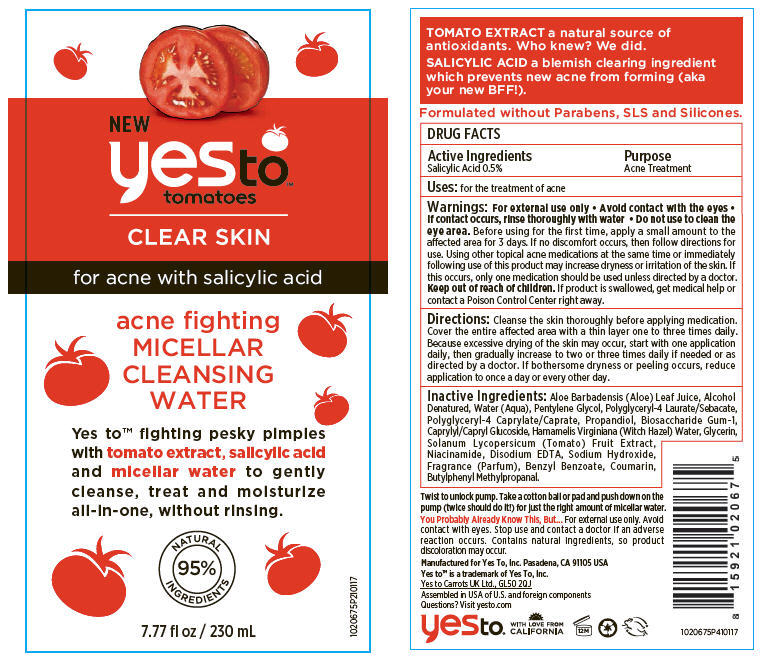 DRUG LABEL: Yes To Tomatoes Micellar Cleansing Water
NDC: 69840-009 | Form: LOTION
Manufacturer: Yes To Incorporated
Category: otc | Type: HUMAN OTC DRUG LABEL
Date: 20170612

ACTIVE INGREDIENTS: Salicylic Acid 5 mg/1 mL
INACTIVE INGREDIENTS: WATER; Pentylene Glycol; POLYGLYCERIN-4; POLYGLYCERYL-4 CAPRATE; GLYCERIN; Biosaccharide Gum-1; CAPRYLYL/CAPRYL OLIGOGLUCOSIDE; WITCH HAZEL; Niacinamide; EDETATE DISODIUM ANHYDROUS; PROPANEDIOL; ALOE VERA LEAF; Alcohol; SOLANUM LYCOPERSICUM FRUITING TOP; SODIUM HYDROXIDE

Yes To™ Tomatoes Micellar Cleansing Water

DRUG FACTS

Active Ingredients

Salicylic Acid 0.5%

Purpose

Acne Treatment

Uses

for the treatment of acne

Warnings

For external use only

- Avoid contact with the eyes
- If contact occurs, rinse thoroughly with water
- Do not use to clean the eye area.

Before using for the first time, apply a small amount to the affected area for 3 days. If no discomfort occurs, then follow directions for use. Using other topical acne medications at the same time or immediately following use of this product may increase dryness or irritation of the skin. If this occurs, only one medication should be used unless directed by a doctor.

Keep out of reach of children. If product is swallowed, get medical help or contact a Poison Control Center right away.

Directions

Cleanse the skin thoroughly before applying medication. Cover the entire affected area with a thin layer one to three times daily. Because excessive drying of the skin may occur, start with one application daily, then gradually increase to two or three times daily if needed or as directed by a doctor. If bothersome dryness or peeling occurs, reduce application to once a day or every other day.

Inactive Ingredients

Aloe Barbadensis (Aloe) Leaf Juice, Alcohol Denatured, Water (Aqua), Pentylene Glycol, Polyglyceryl-4 Laurate/Sebacate, Polyglyceryl-4 Caprylate/Caprate, Propandiol, Biosaccharide Gum-1, Caprylyl/Capryl Glucoside, Hamamelis Virginiana (Witch Hazel) Water, Glycerin, Solanum Lycopersicum (Tomato) Fruit Extract, Niacinamide, Disodium EDTA, Sodium Hydroxide, Fragrance (Parfum), Benzyl Benzoate, Coumarin, Butylphenyl Methylpropanal.

Questions?

Visit yesto.com

PRINCIPAL DISPLAY PANEL - 230 mL Bottle Label

NEW
yesto™
tomatoes

CLEAR SKIN

for acne with salicylic acid

acne fighting
MICELLAR
CLEANSING
WATER

Yes to™ fighting pesky pimples
with tomato extract, salicylic acid
and micellar water to gently
cleanse, treat and moisturize
all-in-one, without rinsing.

NATURAL
95%
INGREDIENTS

7.77 fl oz / 230 mL

1020675P210117